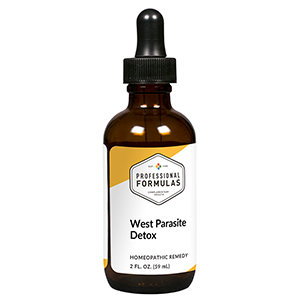 DRUG LABEL: West Parasite Detox
NDC: 63083-6039 | Form: LIQUID
Manufacturer: Professional Complementary Health Formulas
Category: homeopathic | Type: HUMAN OTC DRUG LABEL
Date: 20190815

ACTIVE INGREDIENTS: ANCYLOSTOMA DUODENALE 30 [hp_X]/59 mL; ASCARIS LUMBRICOIDES 30 [hp_X]/59 mL; BLASTOCYSTIS HOMINIS 30 [hp_X]/59 mL; CRYPTOSPORIDIUM HOMINIS 30 [hp_X]/59 mL; DIENTAMOEBA FRAGILIS 30 [hp_X]/59 mL; ECHINOCOCCUS GRANULOSUS 30 [hp_X]/59 mL; ENTAMOEBA HISTOLYTICA 30 [hp_X]/59 mL; ENTEROCOCCUS FAECIUM 30 [hp_X]/59 mL; WUCHERERIA BANCROFTI 30 [hp_X]/59 mL; GIARDIA LAMBLIA 30 [hp_X]/59 mL; ENTEROBIUS VERMICULARIS 30 [hp_X]/59 mL; PLASMODIUM KNOWLESI 30 [hp_X]/59 mL; BANDTOOTH CONGER 30 [hp_X]/59 mL; TRICHOMONAS VAGINALIS 30 [hp_X]/59 mL; TRICHINELLA SPIRALIS 30 [hp_X]/59 mL; TOXOPLASMA GONDII 30 [hp_X]/59 mL
INACTIVE INGREDIENTS: ALCOHOL; WATER

X39

ACTIVE INGREDIENTS

Ancylosotma 30X
Ascaris 30X
Blastocystis hominis 30X
Cryptosporidium 30X
Dientamoeba fragilis 30X
Echinococcinum 30X
Endolimax nana 30X
Entamoeba histolytica 30X
Enterobium 30X
Filarinose 30X
Giardia lamblia 30X
Oxyuren 30X
Plasmodium 30X
Taenia 30X
Trichomonas vaginalis 30X
Trichinella 30X
Toxoplasmosis 30X

QUESTIONS

Professional Formulas

PO Box 2034 Lake Oswego, OR 97035

INDICATIONS

For the temporary relief of mild abdominal pain, nausea or vomiting, diarrhea, coughing or wheezing, difficulty breathing, fatigue, or feelings of discomfort or uneasiness.*

PURPOSE

*Claims based on traditional homeopathic practice, not accepted medical evidence. Not FDA evaluated.

WARNINGS

Persistent symptoms may be a sign of a serious condition. If symptoms persist or are accompanied by a fever, rash, or persistent headache, consult a doctor. Keep out of the reach of children. In case of overdose, get medical help or contact a poison control center right away. If pregnant or breastfeeding, ask a healthcare professional before use.

Keep out of the reach of children.

PREGNANCY OR BREAST FEEDING

If pregnant or breastfeeding, ask a healthcare professional before use.

DIRECTIONS

Place drops under tongue 30 minutes before/after meals. Adults and children 12 years and over: Take 10 drops up to 3 times per day. Consult a physician for use in children under 12 years of age.

OTHER INFORMATION

Tamper resistant. If seal is broken, do not use. After opening, close container tightly and store at room temperature away from heat.

INACTIVE INGREDIENTS

20% ethanol, purified water.

LABEL

Est 1985

Professional Formulas

Complementary Health

West Parasite Detox

Homeopathic Remedy

2 FL. OZ. (59 mL)